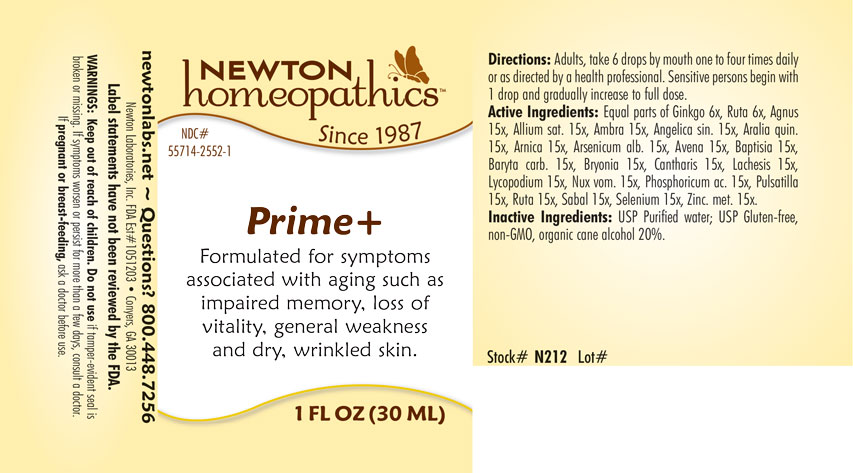 DRUG LABEL: Prime
NDC: 55714-2552 | Form: LIQUID
Manufacturer: Newton Laboratories, Inc.
Category: homeopathic | Type: HUMAN OTC DRUG LABEL
Date: 20250210

ACTIVE INGREDIENTS: PHOSPHORIC ACID 15 [hp_X]/1 mL; GINKGO 6 [hp_X]/1 mL; GARLIC 15 [hp_X]/1 mL; AMBERGRIS 15 [hp_X]/1 mL; ANGELICA SINENSIS ROOT 15 [hp_X]/1 mL; AMERICAN GINSENG 15 [hp_X]/1 mL; ARNICA MONTANA 15 [hp_X]/1 mL; ARSENIC TRIOXIDE 15 [hp_X]/1 mL; AVENA SATIVA FLOWERING TOP 15 [hp_X]/1 mL; BAPTISIA TINCTORIA ROOT 15 [hp_X]/1 mL; BARIUM CARBONATE 15 [hp_X]/1 mL; BRYONIA ALBA ROOT 15 [hp_X]/1 mL; LYTTA VESICATORIA 15 [hp_X]/1 mL; LACHESIS MUTA VENOM 15 [hp_X]/1 mL; LYCOPODIUM CLAVATUM SPORE 15 [hp_X]/1 mL; STRYCHNOS NUX-VOMICA SEED 15 [hp_X]/1 mL; ANEMONE PULSATILLA 15 [hp_X]/1 mL; RUTA GRAVEOLENS FLOWERING TOP 15 [hp_X]/1 mL; SAW PALMETTO 15 [hp_X]/1 mL; SELENIUM 15 [hp_X]/1 mL; ZINC 15 [hp_X]/1 mL; CHASTE TREE FRUIT 15 [hp_X]/1 mL
INACTIVE INGREDIENTS: ALCOHOL; WATER

Prime 2552L

INDICATIONS & USAGE SECTION

Formulated for symptoms associated with aging sucha as impared memory,, loss of vitality, general weakness and dry, wrinkled skin..

DOSAGE & ADMINISTRATION SECTION

Directions: Adults, take 6 drops by mouth one to four times daily or as directed by a health professional. Sensitive persons begin with 1 drop and gradually increase to full dose.

OTC - ACTIVE INGREDIENT SECTION

Equal parts of Ginkgo biloba 6x, Ruta graveolens 6x, Agnus castus 15x, Allium sativum 15x, Ambra grisea 15x, Angelica sinensis radix 15x, Aralia quinquefolia 15x, Arnica montana 15x, Arsenicum album 15x, Avena sativa 15x, Baptisia tinctoria 15x, Baryta carbonica 15x, Bryonia 15x, Cantharis 15x, Lachesis mutus 15x, Lycopodium clavatum 15x, Nux vomica 15x, Phosphoricum acidum 15x, Pulsatilla 15x, Ruta graveolens 15x, Sabal serrulata 15x, Selenium metallicum 15x, Zincum metallicum 15x.

OTC - PURPOSE SECTION

Formulated for symptoms associated with aging such as impared memory, loss of vitality, general weakness and dry, wrinkled skin.

INACTIVE INGREDIENT SECTION

Inactive Ingredients: USP Purified Water; USP Gluten-free, non-GMO, organic cane alcohol 20%.

QUESTIONS SECTION

newtonlabs.net – Questions? 800.448.7256

Newton Laboratories, Inc. FDA Est # 1051203 - Conyers, GA 30013

WARNINGS SECTION

WARNINGS: Keep out of reach of children. Do not use if tamper-evident seal is broken or missing. If symptoms worsen or persist for more than a few days, consult a doctor. If pregnant or breast-feeding, ask a doctor before use.

OTC - PREGNANCY OR BREAST FEEDING SECTION

If pregnant or breast-feeding, ask a doctor before use.

OTC - KEEP OUT OF REACH OF CHILDREN SECTION

Keep out of reach of children.